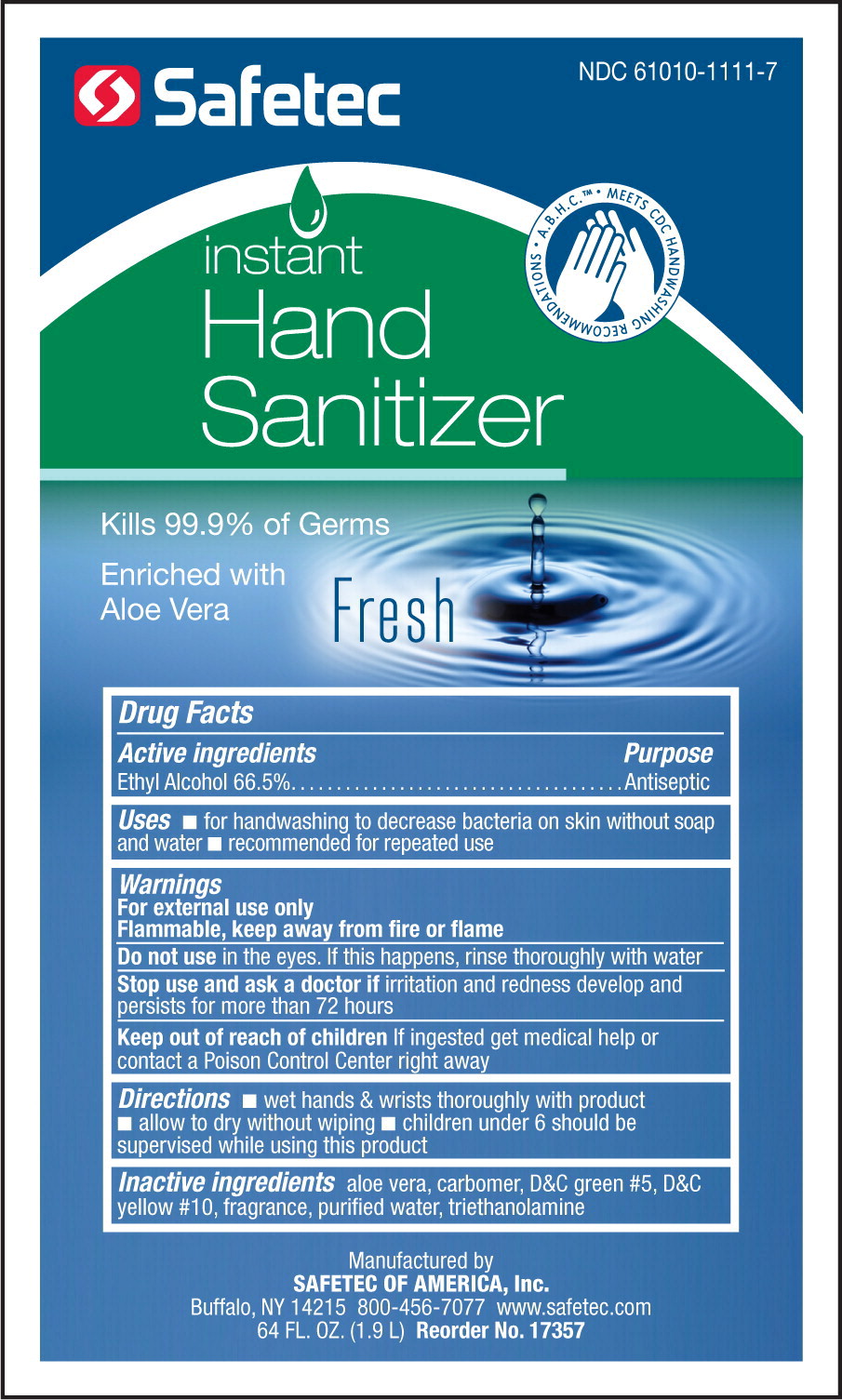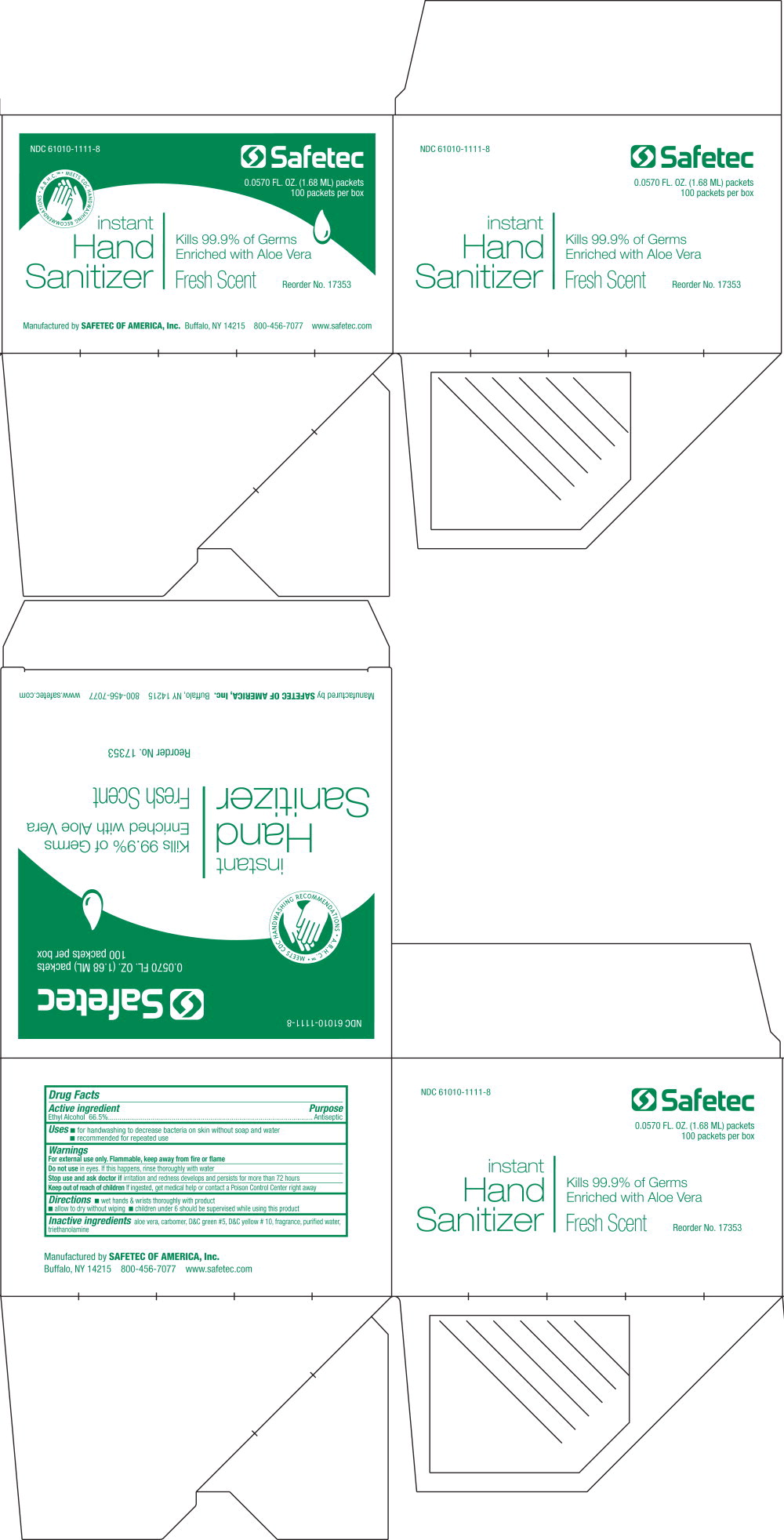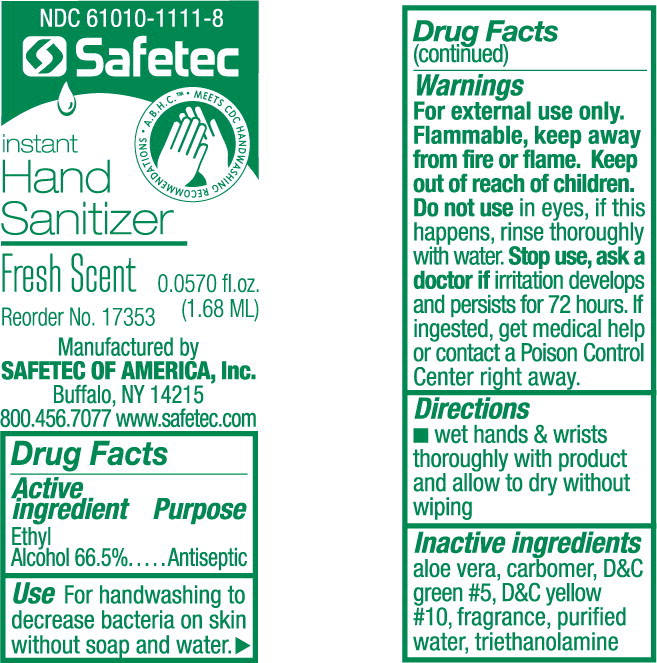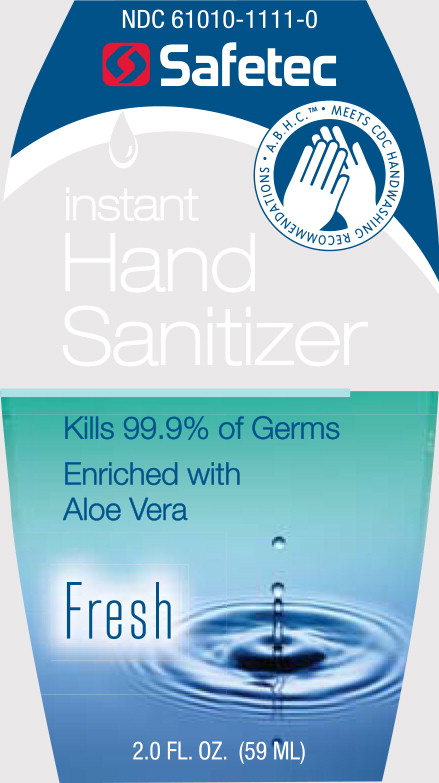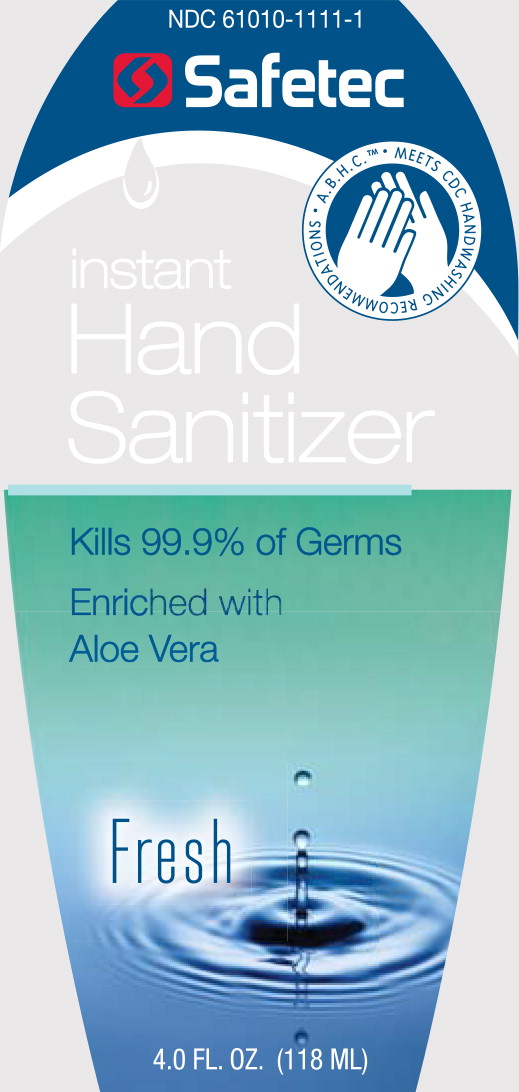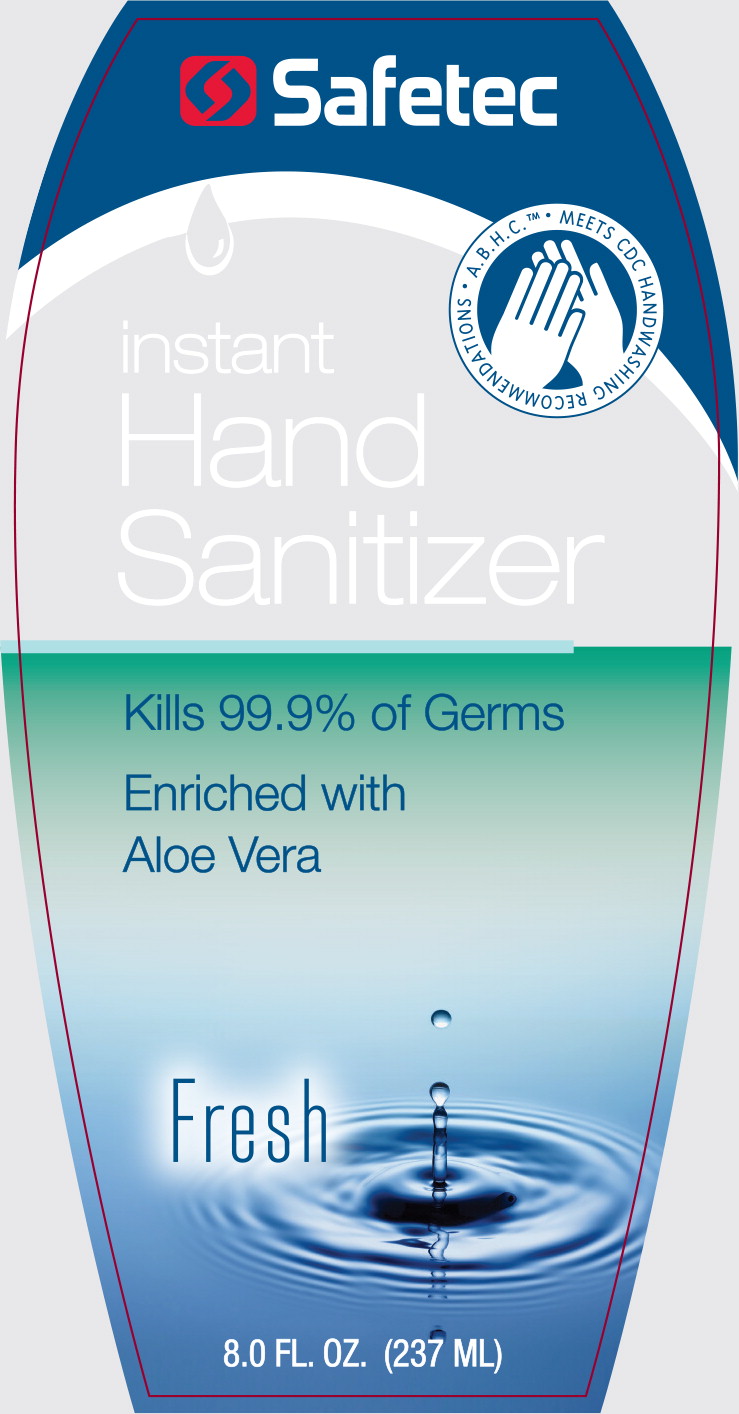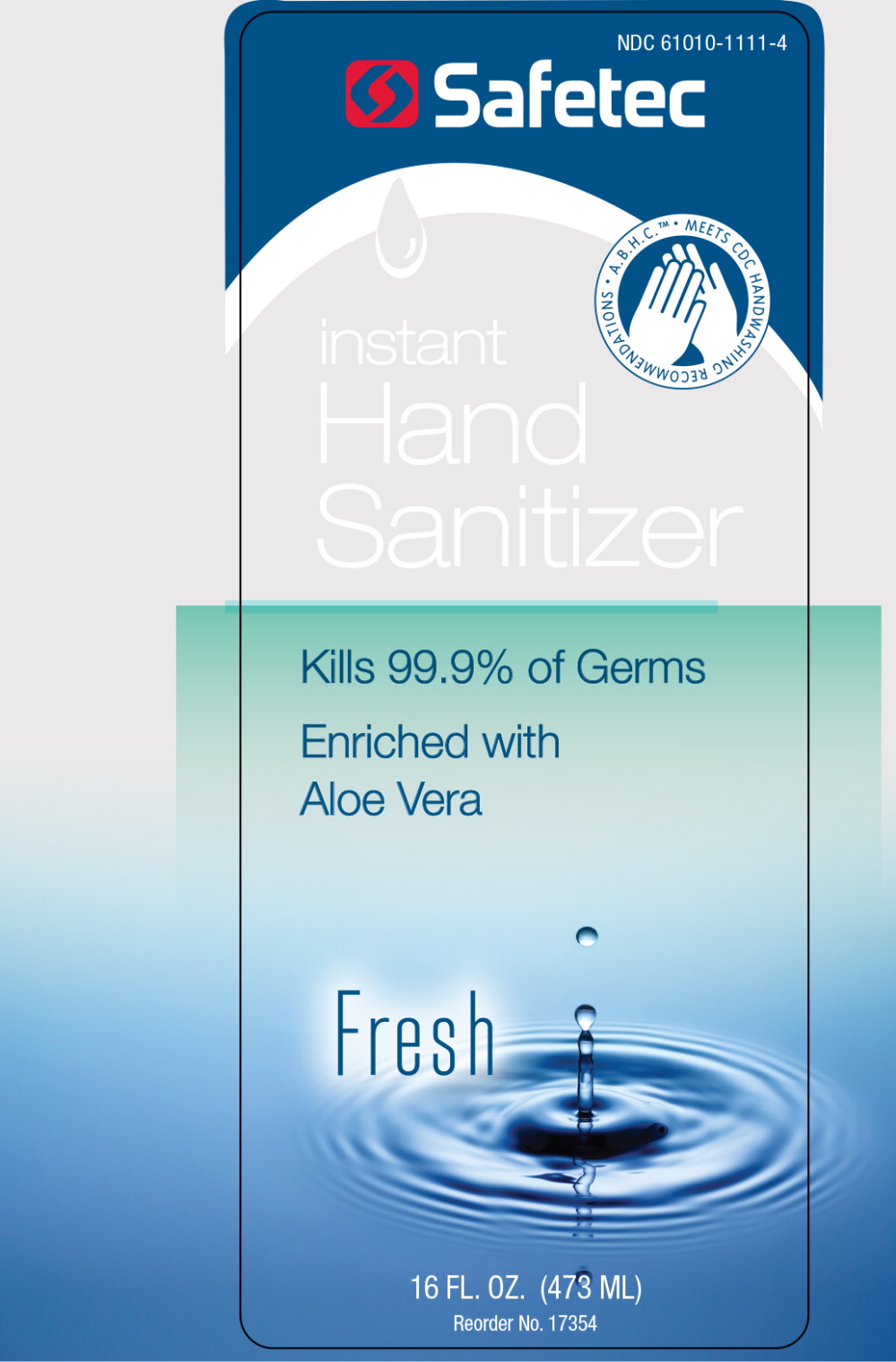 DRUG LABEL: Instant Hand Sanitizer
NDC: 61010-1111 | Form: GEL
Manufacturer: Safetec of America, Inc.
Category: otc | Type: HUMAN OTC DRUG LABEL
Date: 20240212

ACTIVE INGREDIENTS: ALCOHOL
 540.26 g/1 L
INACTIVE INGREDIENTS: ALOE VERA LEAF; CARBOMER INTERPOLYMER TYPE A (ALLYL SUCROSE CROSSLINKED); D&C GREEN NO. 5; D&C YELLOW NO. 10; WATER; TROLAMINE

61010-111, Instant Hand Sanitizer

Active ingredient

Ethyl Alcohol 66.5%

Purpose

Antiseptic

Uses

- for handwashing to decrease bacteria on skin
- recommended for repeated use

Warnings

For external use only

Flammable, keep away from fire or flame

DO NOT USE

Do not usein the eyes. If this happens, rinse thoroughly with water

Stop use and ask a doctor ifirritation and redness develop and persists for more than 72 hours

Keep out of reach of children

If ingested get medical help or contact a Poison Control Center right away

Directions

- wet hands thoroughly with product
- allow to dry without wiping
- children under 6 should be supervised while using this product

Inactive ingredients

aloe vera, carbomer, D&C green #5, D&C yellow #10, fragrance, purified water, triethanolamine

PRINCIPAL DISPLAY PANEL – 1.9 L Bottle Label

NDC 61010-1111-7

Safetec

instant

Hand

Sanitizer

Kills 99.9% of Germs

Enriched with
Aloe Vera
Fresh

Manufactured by
SAFETEC OF AMERICA, Inc.
Buffalo, NY 14215 800-456-7077 www.safetec.com

64 FL. OZ. (1.9 L) Reorder No. 17357

PRINCIPAL DISPLAY PANEL – 0.0570 fl. oz. box

NDC 61010-1111-8

Safetec

instant

Hand

Sanitizer

Kills 99.9% of Germs
Enriched with Aloe Vera
Fresh Scent

0.0570 FL. OZ. (1.68 ML) packets
100 packets per box

Reorder No. 17353

Manufactured by SAFETEC OF AMERICA, Inc.
Buffalo, NY 14215
800-456-7077
www.safetec.com

PRINCIPAL DISPLAY PANEL – 0.0570 fl. oz. packet

NDC 61010-1111-8

Safetec

instant

Hand

Sanitizer

Fresh Scent

0.0570 fl.oz.
(1.68 ML)

Reorder No. 17353
Manufactured by
SAFETEC OF AMERICA, Inc.
Buffalo, NY 14215
800-456-7077 www.safetec.com

Principal Display Panel – 2.0 FL OZ Bottle Panel

NDC 61010-1111-0

Safetec

A.B.H.C.™ MEETS CDC HANDWASHING RECOMMENDATIONS

instant
Hand
Sanitizer

Kills 99.9% of Germs

Enriched with
Aloe Vera

Fresh

2.0 FL. OZ. (59 ML)

Principal Display Panel – 4.0 FL OZ Bottle Panel

NDC 61010-1111-1

Safetec

A.B.H.C.™ MEETS CDC HANDWASHING RECOMMENDATIONS

instant
Hand
Sanitizer

Kills 99.9% of Germs

Enriched with
Aloe Vera

Fresh

4.0 FL. OZ. (118 ML)

Principal Display Panel – 8.0 FL OZ Bottle Panel

Safetec

A.B.H.C.™ MEETS CDC HANDWASHING RECOMMENDATIONS

instant
Hand
Sanitizer

Kills 99.9% of Germs

Enriched with
Aloe Vera

Fresh

8.0 FL. OZ. (237 ML)

Principal Display Panel – 16.0 FL OZ Bottle Panel

NDC 61010-1111-4

Safetec

A.B.H.C.™ MEETS CDC HANDWASHING RECOMMENDATIONS

instant
Hand
Sanitizer

Kills 99.9% of Germs

Enriched with
Aloe Vera

Fresh

16.0 FL. OZ. (473 ML)

Reorder No. 17354